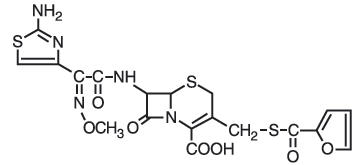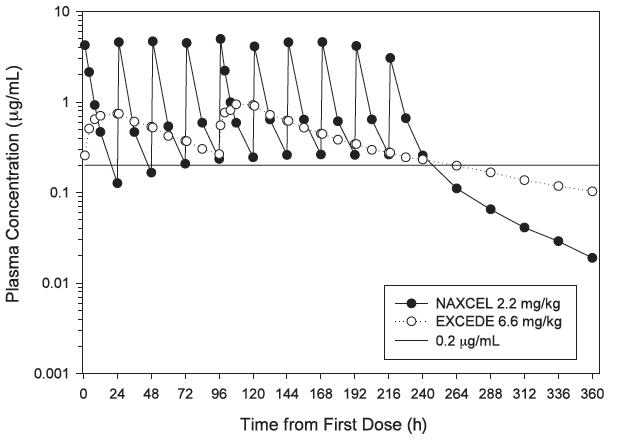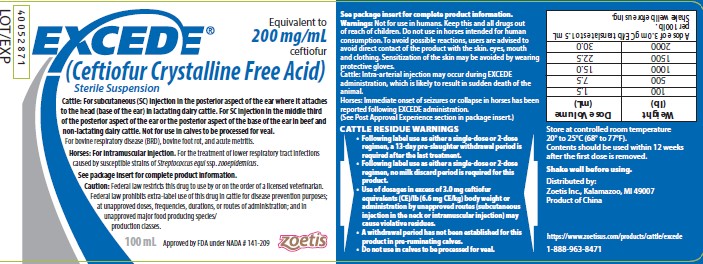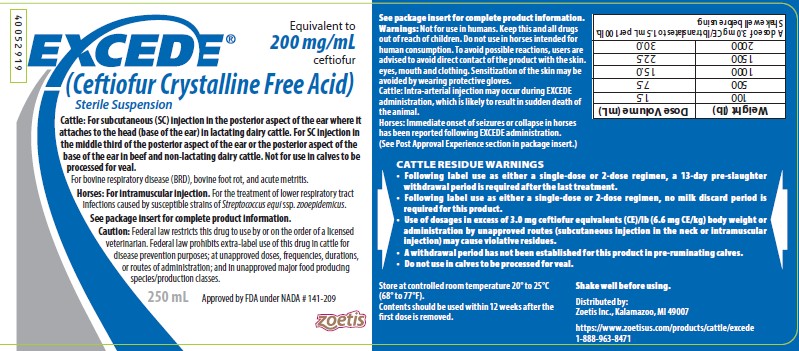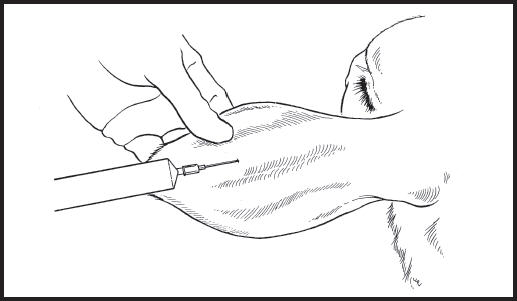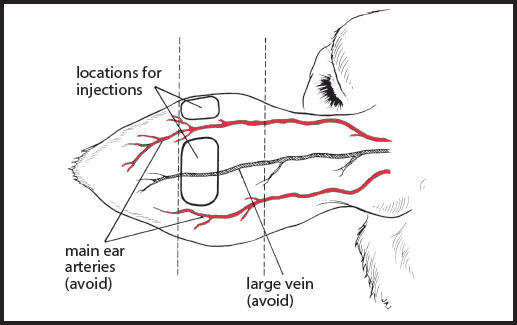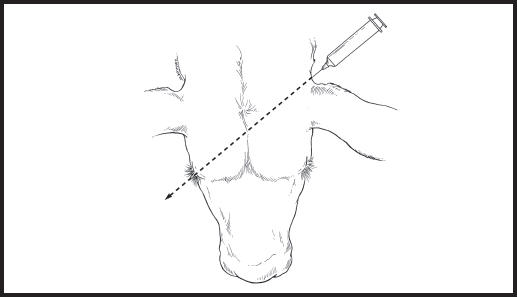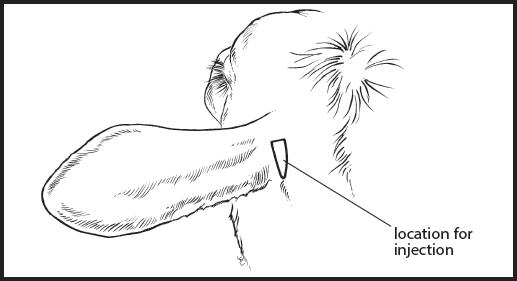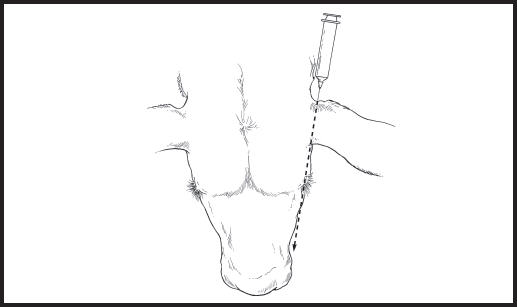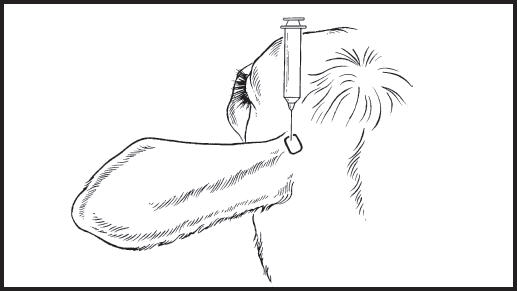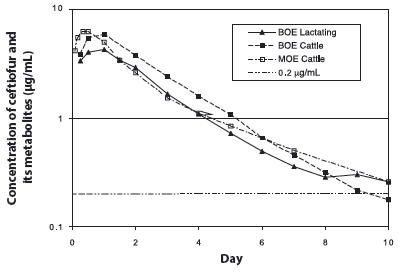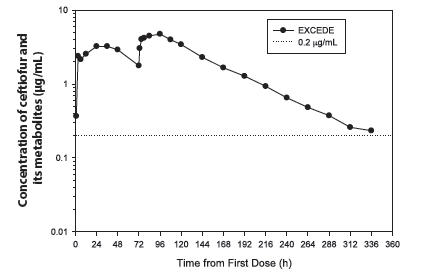 DRUG LABEL: Excede
NDC: 54771-5224 | Form: INJECTION, SUSPENSION
Manufacturer: Zoetis Inc.
Category: animal | Type: PRESCRIPTION ANIMAL DRUG LABEL
Date: 20250813

ACTIVE INGREDIENTS: CEFTIOFUR 200 mg/1 mL

EXCEDE®
(Ceftiofur Crystalline Free Acid)
Sterile Suspension

For subcutaneous injection in the posterior aspect of the ear where it attaches to the head (base of the ear) in lactating dairy cattle. For subcutaneous injection in the middle third of the posterior aspect of the ear or in the posterior aspect of the ear where it attaches to the head (base of the ear) in beef and non-lactating dairy cattle. Not for use in calves to be processed for veal.

CAUTION

Federal law restricts this drug to use by or on the order of a licensed veterinarian.
Federal law prohibits extra-label use of this drug in cattle for disease prevention purposes; at unapproved doses, frequencies, durations, or routes of administration; and in unapproved major food producing species/
production classes.

DESCRIPTION

EXCEDE Sterile Suspension is a ready-to-use formulation that contains the crystalline free acid of ceftiofur, which is a broad spectrum cephalosporin antibiotic active against Gram-positive and Gram-negative bacteria including ß-lactamase-producing strains. Like other cephalosporins, ceftiofur is bactericidal, in vitro, resulting from inhibition of cell wall synthesis.

Each mL of this ready-to-use sterile suspension contains ceftiofur crystalline free acid equivalent to 200 mg ceftiofur, in a caprylic/capric triglyceride and cottonseed oil based suspension.

Figure 1. Structure of ceftiofur crystalline free acid:

Chemical name of ceftiofur crystalline free acid:

7-[[2-(2-Amino-4-thiazolyl)-2-(methoxyimino)acetyl]amino]- 3-[[(2-furanylcarbonyl) thio] methyl]-8-oxo-5-thia-1- azabicyclo[4.2.0]oct-2-ene 2-carboxylic acid

INDICATIONS

EXCEDE Sterile Suspension is indicated for treatment of bovine respiratory disease (BRD, shipping fever, pneumonia) associated with Mannheimia haemolytica, Pasteurella multocida, and Histophilus somni in beef, non-lactating dairy, and lactating dairy cattle.

EXCEDE Sterile Suspension is also indicated for the control of respiratory disease in beef and non-lactating dairy cattle which are at high risk of developing BRD associated with M. haemolytica, P. multocida, and H. somni.

EXCEDE Sterile Suspension is also indicated for the treatment of bovine foot rot (interdigital necrobacillosis) associated with Fusobacterium necrophorum and Porphyromonas levii in beef, non-lactating dairy, and lactating dairy cattle.

EXCEDE Sterile Suspension is also indicated for treatment of acute metritis (0-10 days post-partum) associated with bacterial organisms susceptible to ceftiofur in lactating dairy cattle.

DOSAGE

Treatment of BRD and bovine foot rot

Administer as a single subcutaneous injection in the posterior aspect of the ear where it attaches to the head (base of the ear) to cattle at a dosage of 3.0 mg ceftiofur equivalents (CE)/lb (6.6 mg CE/kg) body weight (BW) (1.5 mL sterile suspension per 100 lb BW).

In beef and non-lactating dairy cattle, EXCEDE Sterile Suspension may also be administered as a single subcutaneous injection in the middle third of the posterior aspect of the ear at a dosage of 3.0 mg CE/lb (6.6 mg CE/kg) BW (1.5 mL sterile suspension per 100 lb BW).

Most animals will respond to treatment within three to five days. If no improvement is observed, the diagnosis should be reevaluated.

Control of BRD

Administer as a subcutaneous injection either in the middle third of the posterior aspect of the ear or in the posterior aspect of the ear where it attaches to the head (base of the ear) to beef and non-lactating dairy cattle at a dosage of 3.0 mg CE/lb (6.6 mg CE/kg) BW (1.5 mL sterile suspension per 100 lb BW).

Clinical studies indicate that administration of EXCEDE Sterile Suspension is effective for the control of respiratory disease in beef and non-lactating dairy cattle at "high risk" of developing BRD. One or more of the following factors typically characterizes calves on arrival at high risk of developing BRD.

- Cattle are from multiple farm origins,
- cattle have had extended transport times (that may have included few if any rest stops),
- ambient temperature change from origin to arrival of 30° F or more,
- cattle have had continued exposure to extremely wet or cold weather conditions,
- cattle have experienced excessive shrink or excessive arrival processing procedures (such as castration, dehorning).

Treatment of Acute Metritis

Administer as a subcutaneous injection in the posterior aspect of the ear where it attaches to the head (base of the ear) to lactating dairy cattle at a dosage of 3.0 mg CE/lb (6.6 mg CE/kg) BW (1.5 mL sterile suspension per 100 lb BW). Repeat this dose in the contra-lateral (opposite) ear approximately 72 hours following the initial dose.

Table 1. Dosing Schedule for EXCEDE Sterile Suspension.
Weight (lb) | Dose Volume (mL) |  | Weight (lb) | Dose Volume (mL)
100 | 1.5 |  | 1100 | 16.5
200 | 3.0 |  | 1200 | 18.0
300 | 4.5 |  | 1300 | 19.5
400 | 6.0 |  | 1400 | 21.0
500 | 7.5 |  | 1500 | 22.5
600 | 9.0 |  | 1600 | 24.0
700 | 10.5 |  | 1700 | 25.5
800 | 12.0 |  | 1800 | 27.0
900 | 13.5 |  | 1900 | 28.5
1000 | 15.0 |  | 2000 | 30.0

ADMINISTRATION

ADMINISTRATION FOR THE MIDDLE THIRD OF THE EAR

- Shake well before using. Please read the complete package insert before administering EXCEDE Sterile Suspension subcutaneously in the posterior ear of cattle.
- Deposit as a single subcutaneous injection in the middle third of the posterior aspect of the ear, avoiding all blood vessels. See Figures 2 and 3.
- Adjust the needle insertion point to avoid any blood vessels, previous implants, ear tags or ear tag holes. Do not administer intra-arterially.
- Deliver the entire contents of the syringe.
- When administered correctly, a subcutaneous bleb of EXCEDE Sterile Suspension will appear.
- When withdrawing the needle, apply pressure to the needle insertion point, and massage toward the base of the ear.

Figure 2. Subcutaneous administration of EXCEDE Sterile Suspension in the middle third of the posterior aspect of the ear.

Figure 3. Diagram of the approximate locations of the major arteries of the posterior ear and the recommended needle insertion locations. Administration of EXCEDE Sterile Suspension into ear arteries is likely to be fatal.

ADMINISTRATION FOR BASE OF THE EAR

In lactating dairy cattle the injection techniques for subcutaneous (SC) injection in the posterior aspect of the ear where it attaches to the head (base of the ear) can be made by the rostral or ventral injection techniques.

In beef and non-lactating dairy cattle the SC injection in the base of the ear can be made by the rostral, ventral or toward the opposite eye injection techniques.

- Shake well before using. Please read the complete package insert before administering EXCEDE Sterile Suspension subcutaneously in the posterior aspect of the ear where it attaches to the head (base of the ear).
- The subcutaneous (SC) injection may be made using the toward the opposite eye, rostral, or ventral techniques. Hold the syringe and needle and insert the needle as described below.
- Deliver the entire contents of the syringe.
- Do not administer EXCEDE Sterile Suspension in the neck.

Administration for the Base of the Ear: Toward the Opposite Eye Technique

- Hold the syringe and needle behind the ear to be dosed so the needle and syringe point in the direction of an imaginary line that would pass through the head toward the animal's opposite eye. See Figures 4 and 5.
- Insert the needle through the loose skin in the posterior aspect of the ear where it attaches to the head (base of the ear) while maintaining this angle. See Figure 4.

Figure 4. Subcutaneous administration of EXCEDE Sterile Suspension in the posterior aspect of the ear where it attaches to the head (base of the ear).

Figure 5. Injection location for the subcutaneous administration of EXCEDE Sterile Suspension in the posterior aspect of the ear where it attaches to the head (base of the ear).

Administration for the Base of Ear: Toward the Same Eye Technique or Rostral Direction

- Hold the syringe and needle behind the ear to be dosed so the needle and syringe point in the direction of an imaginary line that would pass through the head toward the eye on the same side of the head. See Figures 5 and 6.
- Insert the needle through the loose skin in the posterior aspect of the ear where it attaches to the head (base of the ear) while maintaining the needle position. See Figure 6.

Figure 6. Diagram of head showing the direction for the base of ear injections administered rostrally toward the eye on the same side of the head into the loose skin in the caudal aspect of the base of the ear.

Administration for Base of the Ear: Ventral Technique

- Hold the syringe and needle above the ear to be dosed so that the needle and syringe are pointing ventrally toward the base of the ear. The needle will be inserted into the loose skin in the posterior aspect of the ear where it attaches to the head (base of the ear) while pointing ventrally. Care should be taken to not insert the needle through the cartilage of the ear. See Figure 7.
- Insert the needle through the loose skin in the posterior aspect of the ear where it attaches to the head (base of the ear) while maintaining needle position. See Figure 7.

Figure 7. Diagram of head showing the direction of base of ear injections when administered ventrally into the loose skin in the caudal aspect of the base of the ear.

CONTRAINDICATIONS

As with all drugs, the use of EXCEDE Sterile Suspension is contraindicated in animals previously found to be hypersensitive to the drug.

WARNINGS

FOR USE IN ANIMALS ONLY. NOT FOR HUMAN USE.
KEEP OUT OF REACH OF CHILDREN.

Penicillins and cephalosporins can cause allergic reactions in sensitized individuals. Topical exposures to such antimicrobials, including ceftiofur, may elicit mild to severe allergic reactions in some individuals. Repeated or prolonged exposure may lead to sensitization. Avoid direct contact of the product with the skin, eyes, mouth and clothing. Sensitization of the skin may be avoided by wearing protective gloves.
Persons with a known hypersensitivity to penicillin or cephalosporins should avoid exposure to this product.
In case of accidental eye exposure, flush with water for 15 minutes. In case of accidental skin exposure, wash with soap and water. Remove contaminated clothing. If allergic reaction occurs (e.g., skin rash, hives, difficult breathing), seek medical attention.
The material safety data sheet contains more detailed occupational safety information. To obtain a material safety data sheet or to report any adverse event please call 1-888-963-8471.
Intra-arterial injection may occur during administration of EXCEDE Sterile Suspension via middle third of the ear injection or base of the ear injection directed towards the opposite eye. Intra-arterial injection of EXCEDE Sterile Suspension is likely to result in sudden death of the animal.

RESIDUE WARNINGS

- Following label use as either a single-dose or 2-dose regimen, a 13-day pre-slaughter withdrawal period is required after the last treatment.
- Following label use as either a single-dose or 2-dose regimen, no milk discard period is required for this product.
- Use of dosages in excess of 3.0 mg CE/lb (6.6 mg CE/kg) BW or administration by unapproved routes (subcutaneous injection in
  the neck or intramuscular injection) may cause violative residues.
- A withdrawal period has not been established for this product in preruminating calves.
- Do not use in calves to be processed for veal.

ANTIBACTERIAL WARNINGS

Use of antibacterial drugs in the absence of a susceptible bacterial infection is unlikely to provide benefit to treated animals and may increase the risk of the development of drug-resistant bacteria.

PRECAUTIONS

Following subcutaneous injection in the middle third of the posterior aspect of the ear, thickening and swelling (characterized by aseptic cellular infiltrate) of the ear may occur. As with other parenteral injections, localized post-injection bacterial infections may result in abscess formation. Attention to hygienic procedures can minimize their occurrence.
Following injection in the posterior aspect of the ear where it attaches to the head (base of the ear), areas of discoloration and signs of inflammation may persist at least 13 days post administration resulting in trim loss of edible tissue at slaughter. Injection of volumes greater than 20 mL, in the middle third of the ear, may result in open draining lesions in a small percentage of cattle.
The effects of ceftiofur on bovine reproductive performance, pregnancy, and lactation have not been determined.

ADVERSE EFFECTS

Intra-arterial injection may occur during administration of EXCEDE Sterile Suspension via middle third of the ear injection or base of the ear injection directed towards the opposite eye. Intra-arterial injection of EXCEDE Sterile Suspension is likely to result in sudden death of the animal. During the conduct of clinical studies, there was a low incidence of acute death (see ANIMAL SAFETY) confirmed to be the result of inadvertent intra-arterial injection. No other adverse systemic effects were noted for either the antibiotic or formulation during any of the clinical and target animal safety studies.

CLINICAL PHARMACOLOGY

Ceftiofur administered as either ceftiofur sodium (NAXCEL® Sterile Powder), ceftiofur hydrochloride (EXCENEL® RTU Sterile Suspension), or ceftiofur crystalline free acid (EXCEDE Sterile Suspension) is metabolized rapidly to desfuroylceftiofur, the primary metabolite. Subcutaneous administration of ceftiofur crystalline free acid, either in the middle third of the posterior aspect of the ear (middle third of the ear, MOE) of beef and non-lactating dairy cattle, or in the posterior aspect of the ear where it attaches to the head (base of the ear, BOE) of beef, non-lactating dairy, and lactating dairy cattle, provides therapeutic concentrations of ceftiofur and desfuroylceftiofur-related metabolites in plasma above the lowest minimum inhibitory concentration to encompass 90% of the most susceptible isolates (MIC90) for the labeled BRD pathogens, Pasteurella multocida, Mannheimia haemolytica and Histophilus somni, for generally not less than 150 hours after a single administration (See Figure 8).

Single Dose Regimen

The pharmacokinetic parameters for the two subcutaneous locations of injection (MOE and BOE) are found in Table 2. Statistical analyses of the data from these two subcutaneous injection sites (MOE and BOE) demonstrate that they are therapeutically equivalent.

Figure 8. Average (n=12/group) plasma concentrations of ceftiofur and desfuroylceftiofur-related metabolites after administration of EXCEDE Sterile Suspension at 3.0 mg CE/lb (6.6 mg CE/kg) BW via subcutaneous injection into one of two different locations of the ear, middle third of the ear (MOE Cattle) and base of the ear (BOE Cattle) in beef cattle as well into the base of the ear (BOE Lactating) in lactating dairy cattle.

Table 2. Average (n = 12/group) pharmacokinetic parameters for ceftiofur and desfuroylceftiofur metabolites calculated after a single subcutaneous administration of 3.0 mg CE/lb (6.6 mg CE/kg) BW of EXCEDE Sterile Suspension in either the middle third of the ear or the base of the ear.
Pharmacokinetic Parameter | Beef - Middle Third of the Ear Mean Value ± Standard Deviation | Beef - Base of the Ear Mean Value ± Standard Deviation | Dairy Cow - Base of the Ear Mean Value ± Standard Deviation
Cmax (µg CE/mL) | 6.90 ± 2.68 | 6.39 ± 1.79 | 4.44 ± 1.65
tmax (h) | 12.0 ± 6.2 | 19.8 ± 5.81 | 19.00 ± 8.02
AUC 0-LOQ (µg∙h/mL) | 376 ± 66.1 | 412 ± 67.3 | 313 ± 85.5
t>0.2, model (h) | 183 ± 40.8 | NE | NE
t>0.2, nca (h) | 246 ± 48.5 | 218 ± 45.5 | 205 ± 35.7
t1/2 (h) | 62.3 ± 13.5 | 40.7 ± 11.2 | 43.92 ± 9.84
Cmax (µg CE/mL) = maximum plasma concentration (in µg CE/mL).
tmax (h) = the time after injection when Cmax occurs (in hours).
AUC 0-LOQ (µg∙h/mL) = the area under the plasma concentration vs. time curve from time of injection to the limit of quantitation of the assay (0.15 µg CE/mL).
t>0.2, model (h) = the time plasma concentrations remain above 0.2 µg CE/mL (in hours), estimated using compartmental pharmacokinetic techniques.
t>0.2, nca (h) = the time plasma concentrations remain above 0.2 µg CE/mL (in hours), estimated using noncompartmental pharmacokinetic techniques.
t1/2 (h) = terminal phase biological half life (in hours)
NE = Not estimated

Two-Dose Regimen

A two-dose regimen of 6.6 mg CE/kg BW administered 72 hours apart is required for the treatment of acute metritis in lactating cows. The mean plasma concentration vs. time profile for ceftiofur and desfuroylceftiofur-related metabolites for the 2-dose regimen in 12 cows is shown in Figure 9 below. The pharmacokinetic parameters for the 2-dose regimen are provided in Table 3.

Figure 9. LS-Mean DCA Plasma Concentration Time Profile Following Two Subcutaneous Injections of EXCEDE 72 hours apart at a Dose of 3.0 mg CE/lb (6.6 mg CE/kg) BW in 12 lactating cows.

Table 3. Average (n = 12) Pharmacokinetic Parameters Following Two Subcutaneous Injections of EXCEDE Sterile Suspension at a Dose 3.0 mg CE/lb (6.6 mg CE/kg) BW at a 72 Hour Interval.
PK Parameter | Mean ± Standard Deviation
AUC0-LOQ (µg∙h/mL) | 651 ± 119
t½ (h) | 55.7 ± 4.84
t>0.2 (h) | 341 ± 34.0
Tmax (h) | 77.1 ± 33.4
Cmax (µg/mL) | 5.98 ± 2.51

MICROBIOLOGY

Ceftiofur has demonstrated in vitro activity against Mannheimia haemolytica, Pasteurella multocida, and Histophilus somni, three major pathogens associated with BRD, and against Fusobacterium necrophorum and Porphyromonas levii associated with bovine foot rot.

A summary of the susceptibility of BRD and foot rot pathogens is presented in Table 4. BRD isolates were obtained from cattle enrolled in a field study conducted in the United States that were diagnosed with BRD. Foot rot isolates were obtained from cattle enrolled in a field study conducted in the United States and Canada that were diagnosed with foot rot. Susceptibility testing was conducted according to the Clinical and Laboratory Standards Institute (CLSI) M7-A3 and M11-A6 standards for BRD and foot rot isolates, respectively.

Table 4. Ceftiofur minimum inhibitory concentration (MIC) values [The correlation between in vitro susceptibility data and clinical effectiveness is unknown.] of indicated pathogens isolated from cattle with naturally occurring BRD or foot rot.
Indicated pathogen | Year of isolation | Number of isolates | MIC50 [The lowest MIC to encompass 50% and 90% of the most susceptible isolates, respectively.] (μg/mL) | MIC90 (µg/mL) | MIC range (µg/mL)
Mannheimia haemolytica | 1996 to 1997 | 75 | 0.008 | 0.015 | 0.001 to 0.015
Pasteurella multocida | 1996 to 1997 | 43 | 0.004 | 0.004 | 0.001 to 0.015
Histophilus somni | 1996 to 1997 | 11 | 0.004 | 0.004 | 0.002 to 0.015
Fusobacterium necrophorum | 2006 to 2007 | 148 | ≤ 0.25 | 0.5 | ≤ 0.25 to >128
Porphyromonas levii | 2006 to 2007 | 141 | ≤ 0.25 | 2.0 | ≤ 0.25 to 16

Based on pharmacokinetic and clinical effectiveness studies of ceftiofur in cattle after a single administration of 3.0 mg CE/lb (6.6 mg CE/kg) BW and the MIC and susceptibility data, the following breakpoints are recommended for BRD pathogens by CLSI.

Table 5. CLSI-accepted interpretive criteria [These interpretive criteria are only intended for use when CLSI M31-A2 performance standards are used to determine antimicrobial susceptibility. Interpretive criteria for bovine foot rot pathogens have not been established.] for ceftiofur against cattle respiratory pathogens.
Pathogen | Disk potency | Zone diameter (mm) |  |  | MIC breakpoint (µg/mL)
 |  | S | I | R | S | I | R
Mannheimia haemolytica Pasteurella multocida Histophilus somni | 30 µg | ≥ 21 | 18 to 20 | ≤ 17 | ≤ 2.0 | 4.0 | ≥ 8.0
S – Susceptible
I – Intermediate
R – Resistant

EFFECTIVENESS

A field dose confirmation study for the treatment of BRD evaluated the effectiveness of single doses of 2.0 and 3.0 mg CE/lb (4.4 or 6.6 mg CE/kg) BW for the treatment of the bacterial component of BRD under field conditions. All treatments were administered subcutaneously in the middle third of the posterior aspect of the ear. Cattle were clinically evaluated on Days 2 to 4, 14 and 28 and were observed on all other study days. The 3.0 mg CE/lb (6.6 mg CE/kg) BW EXCEDE Sterile Suspension dose significantly (p ≤ 0.05) increased Day 14 treatment success rate, defined as animals that did not require any ancillary treatment and had a rectal temperature of < 104°F, normal respiration index, and had no or mild depression on that day.

The effectiveness of a single dose of EXCEDE Sterile Suspension for the control of BRD in feedlot cattle was evaluated in a nine-location field effectiveness study. In addition to standard processing on arrival at feedlots, cattle (n=3911) considered to be at high risk for BRD were assigned to one of four arrival treatments, including EXCEDE Sterile Suspension at 2.0 or 3.0 mg CE/lb (4.4 or 6.6 mg CE/kg) BW or negative control. Effectiveness evaluation was based on the incidence of clinical BRD within 28 days following arrival processing. Administration of a single dose of EXCEDE Sterile Suspension administered subcutaneously in the middle third of the posterior aspect of the ear at arrival processing significantly reduced the incidence of BRD in high-risk feedlot cattle in the 28-day period after arrival processing compared to negative controls.

Base of the ear administration (beef and non-lactating dairy cattle) and middle third of the ear administration (lactating dairy cattle) were compared to the middle third of the ear pharmacokinetic data for beef and non-lactating dairy cattle and were found to be therapeutically equivalent.

The effectiveness of EXCEDE Sterile Suspension for the treatment of bovine foot rot was evaluated in a six-location field effectiveness study. Cattle diagnosed with bovine foot rot were enrolled and treated with EXCEDE Sterile Suspension, administered by subcutaneous injection in the base of the ear as a single dose of 3.0 mg CE/lb (6.6 mg CE/kg) BW or an equivalent volume of a vehicle control. Cattle were clinically evaluated 7 days post-treatment for treatment success, which was based on defined decreases in lesion, swelling and lameness scores. A total of 169 beef and dairy cattle were included in the analysis. There was a statistically significant difference (p = 0.0054) in treatment success for EXCEDE-treated cattle (58.4%) compared to vehicle-treated control cattle (13.2%).

The effectiveness of EXCEDE Sterile Suspension for the treatment of acute metritis was evaluated in a 15-location field effectiveness study. A total of 1023 cows with a fetid vaginal discharge and a rectal temperature of ≥ 103 °F were enrolled in the study and treated with either a two-dose regimen of EXCEDE (6.6 mg CE/BW) or an equivalent volume of vehicle control, administered approximately 72 hours apart at the base of opposite ears. At 14 days post-treatment, each cow remaining in the study was examined and rectal temperature and vaginal discharge score were recorded. Cows with a non-fetid discharge, and a rectal temperature < 103 °F, and that did not require alternate ("escape") therapy during the 14_day observation period were classified as a cure. The cure rate was significantly higher (p < 0.0001) in EXCEDE-treated cows (362/493, 74.3%) than in vehicle-treated cows (271/489, 55.3%). One cow died 15 to 20 minutes after the second administration of EXCEDE. Necropsy findings determined the probable cause of death to be intra-arterial injection.

ANIMAL SAFETY

Systemic Safety Studies

After parenteral administration, ceftiofur crystalline free acid (as EXCEDE Sterile Suspension), ceftiofur sodium and ceftiofur hydrochloride are rapidly metabolized to desfuroylceftiofur. Therefore, studies conducted with ceftiofur sodium are adequate to evaluate the systemic safety of EXCEDE Sterile Suspension. Results from a five-day tolerance study conducted with ceftiofur sodium in normal feeder calves indicated that ceftiofur was well tolerated at 25 mg CE/lb/day for five consecutive days, approximately 8 times the approved dose of EXCEDE Sterile Suspension 3.0 mg CE/lb (6.6 mg CE/kg) BW. Ceftiofur administered parenterally had no adverse systemic effects.

In a 15-day safety/toxicity study, five steer and five heifer calves per group were administered ceftiofur sodium intramuscularly at 0 (vehicle control), 1, 3, 5 or 10 mg CE/lb/day thus, evaluating up to 3.3 times the approved dose of EXCEDE Sterile Suspension of 3.0 mg CE/lb/day (6.6 mg CE/kg) BW. There were no adverse systemic effects, indicating that ceftiofur has a wide margin of safety when injected intramuscularly into feeder calves. Local tissue tolerance to subcutaneous injection of EXCEDE Sterile Suspension in the posterior ear of cattle was evaluated in a separate study.

The systemic safety of ceftiofur concentrations resulting from product administration at the base of the ear was established via a pharmacokinetic comparison of the two routes of administration (base of the ear versus middle third of the ear). Based upon the results of this relative bioavailability study, it was determined that the two routes of administration are therapeutically equivalent.

To support systemic target animal safety for the 2-dose metritis regimen, five projected daily doses of NAXCEL Sterile Powder (ceftiofur sodium) at 2.2 mg/kg BW were compared pharmacokinetically with EXCEDE administered 2 times at a 72 hour interval at 6.6 mg/kg BW. The peak concentration (Cmax) and the extent of exposure (AUC) after two doses of EXCEDE were statistically no higher than the exposure following five daily doses of NAXCEL Sterile Powder in beef cattle.

Investigation of Intra-Arterial and Intravenous Injection

In approximately 6000 animals enrolled in the BRD clinical studies, nine animals died following injection of EXCEDE Sterile Suspension. All deaths were within 30 minutes of the time of injection. The exact cause was confirmed in three animals. These deaths resulted from inadvertent intra-arterial injection of this oil-based suspension into one of the two major auricular (ear) arteries. Intra-arterial injection at this location resulted in direct administration of the oil-based formulation into the arterial blood supply of the brain resulting in embolism and death.

Since intra-arterial injection was confirmed in three animals that died following injection of EXCEDE Sterile Suspension, the consequences of purposeful intra-arterial injection of EXCEDE Sterile Suspension were investigated in feeder cattle. Two heifers (body weight approximately 225 kg) were given a single 3.0 mg CE/lb (6.6 mg CE/kg) BW bolus dose of EXCEDE Sterile Suspension in the middle auricular artery. Both heifers collapsed immediately and died within approximately eight minutes of injection. Intra-arterial injection of EXCEDE Sterile Suspension in the ear will result in death and must be avoided.

Since subcutaneous injection in the ear may potentially result in inadvertent intravenous administration of an injectable product, the consequences of purposeful intravenous injection of EXCEDE Sterile Suspension were investigated in feeder cattle. Three heifers and three steers (body weight range 197-223 kg) were given a single 3.0 mg CE/lb (6.6 mg CE/kg) BW bolus dose of EXCEDE Sterile Suspension in the jugular vein and were monitored for adverse effects following injection. One steer and one heifer had transient (2 to 5 minutes) increases in heart rate without any other untoward signs in these or the other cattle. Intravenous injection of EXCEDE Sterile Suspension is an unacceptable route of administration.

Safety Studies in Beef Cattle

Middle of the ear injection:

A study was designed and conducted to specifically address tissue tolerance in cattle when EXCEDE Sterile Suspension was administered as a single subcutaneous injection into the posterior aspect of the ear of cattle at the recommended dose of 3.0 mg CE/lb (6.6 mg CE/kg) BW. Results from this study indicate that the subcutaneous injection of EXCEDE Sterile Suspension into the middle third of the posterior aspect of the ear of cattle is well tolerated and characterized by a biphasic thickening of the ear. The initial increase in thickness is attributed to the space required for the volume of injected material. Additional increases in thickness were observed through Day 14 after injection. After Day 14, post injection ear thickness decreased in all animals. One animal carried an injected ear in a drooping position for 7 days post injection. At necropsy, subcutaneous areas of discoloration and some foci of hemorrhage were observed in ears of injected cattle. The discoloration was markedly reduced in size by the end of the study. Ears are inedible tissues in the US (9 CFR 301.2). No signs of irritation were observed on the edible portions of the carcass around the base of the ear.

The local tolerance of the ear of cattle to a single subcutaneous injection of EXCEDE Sterile Suspension was also evaluated in a large multi-location effectiveness study. None of the 1927 animals treated with EXCEDE Sterile Suspension were removed from this trial due to ear irritation although swelling was noted at some injection sites. Leak back and/or bleeding from the injection site was observed in a small fraction of the treated animals immediately after administration. It was concluded that administration of EXCEDE Sterile Suspension in the posterior aspect of the ear was well tolerated and was acceptable under feedlot conditions.

A study evaluated the 56-day feedlot performance of beef steers administered EXCEDE Sterile Suspension alone, EXCEDE Sterile Suspension with a growth promoting implant, growth promoting implant alone, or neither product, in a total of 207 Angus and Angus cross-bred steers. The administration of EXCEDE Sterile Suspension in the posterior aspect of the ear with or without growth promoting implants was well tolerated by cattle and did not adversely affect feedlot cattle performance. Based upon the results of this study, the location of implants administered after EXCEDE Sterile Suspension may need to be adjusted slightly within the boundaries of the middle third of the ear in some animals.

Base of the ear injection:

The local tolerance of the ear to a single subcutaneous injection at the base of the ear of EXCEDE Sterile Suspension was evaluated in a multi-location field study in 2926 beef cattle. Normal restraint was adequate for administration of EXCEDE Sterile Suspension for 99.8% of cattle. No post injection problems (excessive bleeding or leak back) were observed in 99.8% of cattle. On Days 28 and 56 post-injection, 97.8% and 98.9% of the cattle had "normal" (no observed swelling) ears.

In a residue study, 72 beef cattle were injected in the base of the ear with EXCEDE Sterile Suspension at a dose rate of 3.0 mg CE/lb (6.6 mg CE/kg) BW. Injection sites were observed daily from treatment to necropsy (4, 7, 10, or 13 days post-injection) for swelling and drooping, and evaluated grossly at necropsy, using skinning and trimming procedures similar to slaughterhouse practices. All animals had injection site swelling during the study; swelling resolved prior to euthanasia in 23 of 72 animals. None of the animals showed ear drooping. At necropsy, signs of inflammation (hemorrhage, congestion, and firmness of tissue) and presence of drug material were seen in the area around the injection site and on the carcass. At 13 days post-injection, gross lesions were found in the inedible portions of the base of the ear in all 18 animals, and in the exposed carcass tissue in 11 of 18 animals.

The ventral base of the ear injection technique was evaluated in a conditions of use study in 200 beef cattle. Each animal received a single injection of EXCEDE Sterile Suspension at a dose of 6.6 mg CE/kg BW at the base of the ear using the ventral injection technique. Normal restraint was adequate for 95.5% of animals in the study. Injection site scores were normal for 65.3% and 92.5% of cattle on Days 14 and 28, respectively. One animal had an unusually large swelling on Day 7 which reduced to a size comparable to other study animals by Day 14.

Safety Studies in Lactating Dairy Cattle

The local tolerance of the ear to a single subcutaneous injection at the base of the ear of EXCEDE Sterile Suspension was evaluated in a multi-location field study in 114 adult dairy cattle. Successful injection in the base of the ear was achieved in 97.4% of cattle using normal facilities and restraint equipment. No leak back or excessive bleeding was observed following injection for 99.1% of cattle, with injection volumes ranging from 15 to 30 mL. On Days 28 and 56 following injection of EXCEDE Sterile Suspension in the base of the ear, 95.6% and 100% of ears, respectively, were observed as normal with no injection site swelling.

In a residue study, six dairy cows were injected in the base of the ear at a dose rate of 3.0 mg CE/lb (6.6 mg CE/kg) BW of EXCEDE Sterile Suspension. No animals exhibited drooping ears at any time after treatment but all animals had signs of swelling at the injection site at all observation times after treatment. Cows were slaughtered 10 days after injection. At necropsy, all six cows showed evidence of injection site inflammation (discoloration of fat tissue/fascia) and four of six cows had discoloration of tissue dorsal and posterior to the ear canal on the carcass. In addition to discoloration, tan nodules and a milky white fluid exudate were also present at the sectioned surface.

Injection site safety for base of the ear administration was evaluated in the metritis effectiveness study described above. Normal restraint was adequate for ≥ 97.8% of injections administered. Injection site scores were normal in 50.3%, 73.2%, and 96.4% at 2 or 3, 11, and 54±3 days after the second injection, respectively.

The ventral and rostral base of the ear injection techniques were compared with the toward the opposite eye technique in a conditions of use study in 197 lactating dairy cattle. Normal restraint was adequate for 89.8% (ventral), 98% (rostral), and 100% (opposite eye) of animals in the study. Injection site scores were normal for 32% (rostral), 46.9% (ventral), and 47.9% (opposite eye) of cattle on Day 14, and 73% (rostral), 87.8% (ventral), and 64.6% (opposite eye) of cattle on Day 28, respectively.

TISSUE AND MILK RESIDUE DEPLETION

A radiolabeled residue metabolism study established tolerances for ceftiofur residues in cattle kidney, liver and muscle. A separate study established the tolerance for ceftiofur residues in milk. The tolerances for ceftiofur residues are 0.4 ppm in kidney, 2.0 ppm in liver, 1.0 ppm in muscle and 0.1 ppm in milk.
A pivotal tissue residue decline study was conducted in dairy cattle. In this study, cows received a single injection of 3.0 mg CE/lb (6.6 mg CE/kg) BW. Ceftiofur residues in tissues were less than the tolerances for ceftiofur residues in tissues such as the kidney, liver and muscle by 13 days after dosing. These data collectively support a 13‑day pre-slaughter withdrawal period.
A pivotal milk residue decline study was conducted in lactating dairy cattle. In this study, cows received a single injection of 3.0 mg CE/lb (6.6 mg CE/kg) BW. Ceftiofur residues in milk were less than tolerances at all time points after treatment. These data collectively support that no milk discard period is required for this product.

Two-Dose Residue Decline Studies
A pivotal tissue residue decline study was conducted in dairy cattle. In this study, cows received two injections of 3.0 mg CE/lb (6.6 mg CE/kg) BW with a 72 hour interval between injections. Ceftiofur residues in tissues were less than the tolerances for ceftiofur residues in the kidney by 13 days after the second dose. These data collectively continue to support a 13-day pre-slaughter withdrawal period after the last dose.
A pivotal milk residue decline study was conducted in lactating dairy cattle. In this study, cows received two injections of 3.0 mg CE/lb (6.6 mg CE/kg) BW with a 72 hour interval between injections. Milk residue decline data from this study supports that no milk discard period is required for this product.

STORAGE CONDITIONS

Store at controlled room temperature 20° to 25°C (68° to 77°F). Shake well before using. Contents should be used within 12 weeks after the first dose is removed.

HOW SUPPLIED

EXCEDE Sterile Suspension is available in the following package sizes:

100 mL vial
250 mL vial

Approved by FDA under NADA # 141-209
zoetis
Distributed by:
Zoetis Inc.
Kalamazoo, MI 49007
https://www.zoetisus.com/products/cattle/excede
1-888-963-8471
Revised: May 2025
40052974

See other side for instructions for use in cattle.

For intramuscular injection in the horse.

CAUTION

Federal law restricts this drug to use by or on the order of a licensed veterinarian. Federal law prohibits extra-label use of this drug in cattle for disease prevention purposes; at unapproved doses, frequencies, durations, or routes of administration; and in unapproved major food producing species/production classes.

DESCRIPTION

EXCEDE Sterile Suspension is a ready-to-use formulation that contains the crystalline free acid of ceftiofur, which is a broad spectrum cephalosporin antibiotic active against Gram-positive and Gram-negative bacteria including ß-lactamase-producing strains. Like other cephalosporins, ceftiofur is bactericidal, in vitro, resulting from inhibition of cell wall synthesis.

Each mL of this ready-to-use sterile suspension contains ceftiofur crystalline free acid equivalent to 200 mg ceftiofur, in a caprylic/capric triglyceride and cottonseed oil based suspension.

Figure 1. Structure of ceftiofur crystalline free acid:

Chemical name of ceftiofur crystalline free acid:

7-[[2-(2-Amino-4-thiazolyl)-2-(methoxyimino)acetyl]amino]- 3-[[(2-furanylcarbonyl)thio] methyl]-8-oxo-5-thia-1- azabicyclo[4.2.0]oct-2-ene 2-carboxylic acid

INDICATION

EXCEDE Sterile Suspension is indicated for the treatment of lower respiratory tract infections in horses caused by susceptible strains of Streptococcus equi ssp. zooepidemicus.

DOSAGE AND ADMINISTRATION

Shake well before using.

Administer two intramuscular injections to horses, 4 days apart, at a dose of 3.0 mg/lb (6.6 mg/kg). A maximum of 20 mL per injection site may be administered. Therapeutic drug concentrations are maintained for 6 days after the second injection (or a total of 10 days from the beginning of treatment) against Streptococcus equi ssp. zooepidemicus.

Table 1. Dosing Schedule for EXCEDE Sterile Suspension.
Weight (lb) | Dose Volume (mL) |  | Weight (lb) | Dose Volume (mL)
100 | 1.5 |  | 1100 | 16.5
200 | 3.0 |  | 1200 | 18.0
300 | 4.5 |  | 1300 | 19.5
400 | 6.0 |  | 1400 | 21.0
500 | 7.5 |  | 1500 | 22.5
600 | 9.0 |  | 1600 | 24.0
700 | 10.5 |  | 1700 | 25.5
800 | 12.0 |  | 1800 | 27.0
900 | 13.5 |  | 1900 | 28.5
1000 | 15.0 |  | 2000 | 30.0

CONTRAINDICATIONS

EXCEDE Sterile Suspension is contraindicated in horses with known allergy to ceftiofur or to ß-lactam (penicillins and cephalosporins) group antimicrobials. Due to the extended exposure in horses, based on the drug's pharmacokinetic properties, adverse reactions may require prolonged care.

Warnings and Precautions

Human Safety Warnings
Not for use in humans. For use in animals only. Keep this and all drugs out of reach of children.
Consult a physician in case of accidental human exposure. Penicillins and cephalosporins can cause allergic reactions in sensitized individuals. Topical exposure to such antimicrobials, including ceftiofur, may elicit mild to severe allergic reactions in some individuals. Repeated or prolonged exposure may lead to sensitization. Avoid direct contact of the product with the skin, eyes, mouth and clothing. Sensitization of the skin may be avoided by wearing protective gloves. Persons with a known sensitivity to penicillin or cephalosporins should avoid exposure to this product. In the case of accidental eye exposure, flush with water for 15 minutes. In case of accidental skin exposure, wash with soap and water. Remove contaminated clothing. If allergic reaction occurs (e.g. skin rash, hives, difficult breathing) seek medical attention.

Animal Safety Warnings and Precautions

Immediate onset of seizures or collapse have been reported following Excede administration.
The injection of EXCEDE Sterile Suspension in the horse may cause firmness, swelling, sensitivity, and/or edema at the injection site.
Injection site reactions may be extensive and require veterinary care.
The administration of antimicrobials to horses under conditions of stress may be associated with acute diarrhea that can be fatal. If acute diarrhea is observed, additional doses of EXCEDE should not be administered and appropriate therapy should be initiated.
Due to the extended exposure in horses, based on the drug's pharmacokinetic properties, adverse reactions may require prolonged care. EXCEDE is slowly eliminated from the body, with approximately 17 days needed to eliminate 97% of the dose from the body. Animals experiencing adverse reactions may need to be monitored for this duration of time.
The use of ceftiofur has not been evaluated in horses less than 4 months of age and in breeding, pregnant, or lactating horses. The long term effects on injection sites have not been evaluated.
(See Animal Safety and Post Approval Experience sections)

Antibacterial Warnings

Use of antibacterial drugs in the absence of a susceptible bacterial infection is unlikely to provide benefit to treated animals and may increase the risk of the development of drug-resistant bacteria.

ADVERSE REACTIONS

Pre-Approval Experience:
A total of 373 horses of various breeds, ranging in age from 4 months to 20 years, were included in the field study safety analysis. Adverse reactions reported in horses treated with EXCEDE and the placebo control are summarized in Table 2.
Injection site swelling (edema) was reported in 10 of 278 (3.6%) EXCEDE-treated horses and 1 of 95 (1 %) of the placebo-treated horses. Of the 10 EXCEDE-treated horses with injection site swelling, 8 horses had swellings of 4 cm or less in diameter, one horse had a 10 cm diameter swelling and one horse had injection site reactions to both injections measuring 25 x 12 cm each. The injection site reactions in EXCEDE treated horses resolved over 1 to 20 days.
At least one episode of diarrhea, loose, soft, or cowpie stools were observed in 25 of 278 (9%) of the EXCEDE-treated horses and 7 of 95 (7%) of the placebo-treated horses. The duration of episodes in EXCEDE-treated horses ranged from a single observation of loose stool to observations lasting 6 days. All cases were self-limiting and resolved with minimal (a single dose of loperamide) or no treatment.

Table 2. Number of Horses with Adverse Reactions During the Field Study with EXCEDE.
Adverse Reaction | EXCEDE (n=278) | Placebo (n=95)
Diarrhea/Soft Stool | 25 (9%) | 7 (7%)
Injection Site Swelling | 10 (4%) | 1 (1%)

Post Approval Experience (2019):
The following adverse events are based on post-approval adverse drug experience reporting for Excede. Not all adverse events are reported to FDA/CVM. It is not always possible to reliably estimate the adverse event frequency or establish a causal relationship to product exposure using these data.
The following adverse events for horses are listed in decreasing order by system and decreasing order within system classes.
Injection site reactions: swelling, pain, inflammation, infection, necrosis, muscle stiffness, fibrosis, injection site stiffness/ reluctance to move, hair change, lameness, granuloma.
Systemic: fever, lethargy, edema at locations other than injection site, anorexia.
Gastrointestinal: colic, diarrhea.
Neurologic: ataxia, muscle tremor, seizure, loss of consciousness.
Immune (Allergic reactions): anaphylaxis, urticaria, allergic edema (face, face and neck, lip, or limb edema).
In some cases, death has been reported as an outcome of the adverse events listed above. Sudden death (within minutes), or the immediate onset of seizures or collapse, followed by death or euthanasia, have been reported.
To report suspected adverse events, for technical assistance or to obtain a copy of the Safety Data Sheet (SDS) contact Zoetis, Inc. at (888) 963-8471. For additional information about adverse drug experience reporting for animal drugs, contact FDA at 1-888-FDA-VETS or online at http://www.fda.gov/reportanimalae.

CLINICAL PHARMACOLOGY

Ceftiofur is a beta-lactam antibiotic from the cephalosporin class. Beta lactams exert their inhibitory effect by interfering with bacterial cell wall synthesis. This interference is primarily due to its covalent binding to the penicillin-binding proteins, which are essential for synthesis of the bacterial wall. Ceftiofur administered as either ceftiofur sodium (NAXCEL® Sterile Powder) or ceftiofur crystalline free acid (EXCEDE Sterile Suspension) is rapidly metabolized to desfuroylceftiofur, the primary metabolite with antimicrobial activity. Two intramuscular injections of EXCEDE Sterile Suspension at a dose of 6.6 mg/kg body weight in the horse provide concentrations of ceftiofur and desfuroylceftiofur related metabolites in plasma above the therapeutic target of 0.2 µg/mL for the entire 96 hour (4 day) dosing interval and for 6 days after the second injection (or a total of 10 days from the beginning of treatment) (see Figure 2 and Table 3).

Figure 2. Average plasma concentration of ceftiofur and desfuroylceftiofur related metabolites in horses following the intramuscular administration of either EXCEDE Sterile Suspension at a dose of 3.0 mg/lb (6.6 mg/kg) administered twice at a 96 hour interval or NAXCEL Sterile Powder at a dose of 1.0 mg/lb (2.2 mg/kg BW) once daily for 10 consecutive days.

Table 3. Pharmacokinetic parameters measured after either two intramuscular injections of EXCEDE Sterile Suspension at a dose of 3.0 mg/lb (6.6 mg/kg) BW at a 96 hour interval or NAXCEL Sterile Powder at a dose of 1.0 mg/lb (2.2 mg/kg) BW once daily for 10 consecutive days are summarized in the following table.
PK Parameter | CCFA-SS at 6.6 mg/kg BW administered twice 96 h apart (Mean ± SD; n=12) |  | Ceftiofur sodium at 2.2 mg/kg BW once daily for 10 days (Mean ± SD; n=11)
AUC0-∞ (µg∙h/mL) | 157 (19.1) |  | 353 (44.9)
t>0.2 (h) | 262 (29.0) |  | ND
 | Dose 1 | Dose 2 | Dose 1 | Dose 10
Tmax (h) | 21.6 (5.8) | 15.6 (6.3) | 1.0 | 2.0 (3.3)
Cmax (µg/mL) | 0.78 (0.19) | 1.0 (0.24) | 4.31 ± 0.78 | 3.99 (1.23)

MICROBIOLOGY

Ceftiofur is a cephalosporin antibiotic. Like other ß-lactam antimicrobials, ceftiofur exerts its inhibitory effect by interfering with bacterial cell wall synthesis. This interference is primarily due to its covalent binding to the penicillin-binding proteins (PBPs) (i.e., transpeptidase and carboxypeptidase), which are essential for synthesis of the bacterial wall. Ceftiofur is not active against Pseudomonas spp. and enterococci.

The minimum inhibitory concentration (MIC) values for ceftiofur against label-claim pathogens isolated from lower respiratory tract infections in horses enrolled in a 2007-2008 field effectiveness study are presented in Table 4. All MICs were determined in accordance with the Clinical and Laboratory Standards Institute (CLSI) standards.

Table 4. Activity of EXCEDE Against Pathogens Isolated from Horses Treated With EXCEDE in Field Studies in the U.S. During 2007-2008.
Disease | Pathogen | Treatment Outcome | # of Isolates | Time of Sample Collection | MIC50 µg/mL | MIC90 µg/mL | MIC Range µg/mL
Lower Respiratory Tract Infection | Streptococcus equi ssp. zooepidemicus | Success | 93 [One horse cultured Staphylococcus aureus (successfully treated) and is not represented in the table.] | Pre-Treatment | 0.06 | 0.12 | 0.03-0.5
Lower Respiratory Tract Infection | Streptococcus equi ssp. zooepidemicus | Failure | 42 | Pre-Treatment | 0.06 | 0.25 | 0.03-0.5

EFFECTIVENESS

A double masked, randomized, negative control, field study evaluated the effectiveness of two intramuscular doses of 6.6 mg/kg EXCEDE Sterile Suspension administered 4 days apart for the treatment of lower respiratory infections caused by Streptococcus equi ssp. zooepidemicus in the horse. In this study, a total of 278 horses were treated with EXCEDE, and 95 horses were treated with saline injections. One hundred ninety-three horses (136 EXCEDE and 57 saline placebo) were included in the statistical analysis. Therapeutic success was characterized by no worsening of clinical signs at Day 4, clinical improvement at Day 9, resolution of the clinical signs by Day 15, and no recurrence of clinical signs by Day 25 after initial dosing. EXCEDE was superior to the saline control. Table 5 summarizes the clinical success rates obtained 15 and 25 days after the first dose.

Table 5. Clinical success rates at Day 15 and 25.
Effectiveness parameter | EXCEDE | Saline Control | P-value
Clinical success Day 15 | 73.53% | 38.60% | N/A
Clinical success Day 25 | 69.12% | 31.58% | 0.0215

ANIMAL SAFETY

Two studies, a target animal safety (TAS) study and a pharmacokinetic (PK) study (see CLINICAL PHARMACOLOGY section), were conducted to assess the safety of EXCEDE in the horse.

In the TAS study, healthy adult horses received 6 intramuscular (lateral neck) injections of EXCEDE Sterile Suspension at doses of either 3.0 (1×), 6.0 (2×) or 9.0 (3×) mg/lb with a 4 day interval between each injection. In the TAS study, there were no treatment related gastrointestinal findings for the three EXCEDE Sterile Suspension treatment groups. In the PK study, one horse treated with 6.0 mg/lb (2×) EXCEDE experienced a mild episode of colic the day after the second injection of EXCEDE. The horse recovered without treatment.

Injection sites were observed in both studies. In both studies, the largest injection volume administered was 20 mL per injection site. There were no observations of erythema, necrosis or drainage at the injection sites in these studies. Firmness, swelling, and/or sensitivity were observed in at least one injection site in all horses treated at the label dose. In the TAS study, injection site reaction measurements ranged from no measurable reaction to 16 × 33 × 1.5 cm. In the PK study, the largest area of edema associated with the injection site ranged from no detectable reaction to a 30 × 36 cm area of edema. Injection site reactions developed within 2 days of injection and resolved within 1-18 days. In the PK study, 2 horses had small areas of firmness that had not resolved at the end of the study (21 days after injection). In both studies, a greater incidence of injection site reactions occurred after the second injection, and in several horses, swelling at the injection site resolved then recurred 1-5 days later.

In the PK study, several horses developed clinical signs consistent with foot pain (stiff in the front limbs when turned in tight circles, and increased pulses and heat to the front feet). One horse in the NAXCEL group and one horse in the 6.0 mg/lb (2×) EXCEDE group were euthanized due to laminitis. Clinical signs of foot pain (stiff front limbs and increased heat and pulses in feet) affected more horses, for a longer period of time, in all EXCEDE-treated groups as compared to the NAXCEL-treated group. The study housing (multi-horse pens on concrete slabs) and diet (free choice alfalfa/grass mix and once a day pellets) may have contributed to the development of foot pain. The prevalence and severity of injection site reactions in EXCEDE-treated horses may also have contributed to the development of a stiff gait. A causal relationship between ceftiofur and foot pain could not be definitively determined.

STORAGE CONDITIONS

Store at controlled room temperature 20° to 25°C (68° to 77°F). Shake well before using. Contents should be used within 12 weeks after the first dose is removed.

HOW SUPPLIED

EXCEDE Sterile Suspension is available in the following package sizes:

100 mL vial
250 mL vial

Approved by FDA under NADA # 141-209
zoetis
Distributed by:
Zoetis Inc.
Kalamazoo, MI 49007
https://www.zoetisus.com/products/cattle/excede
1-888-963-8471
Revised: May 2025
40052974

PRINCIPAL DISPLAY PANEL - 100 mL Vial label

100mL label

40052871

PRINCIPAL DISPLAY PANEL - 250 mL Vial label

250mL label

40052919